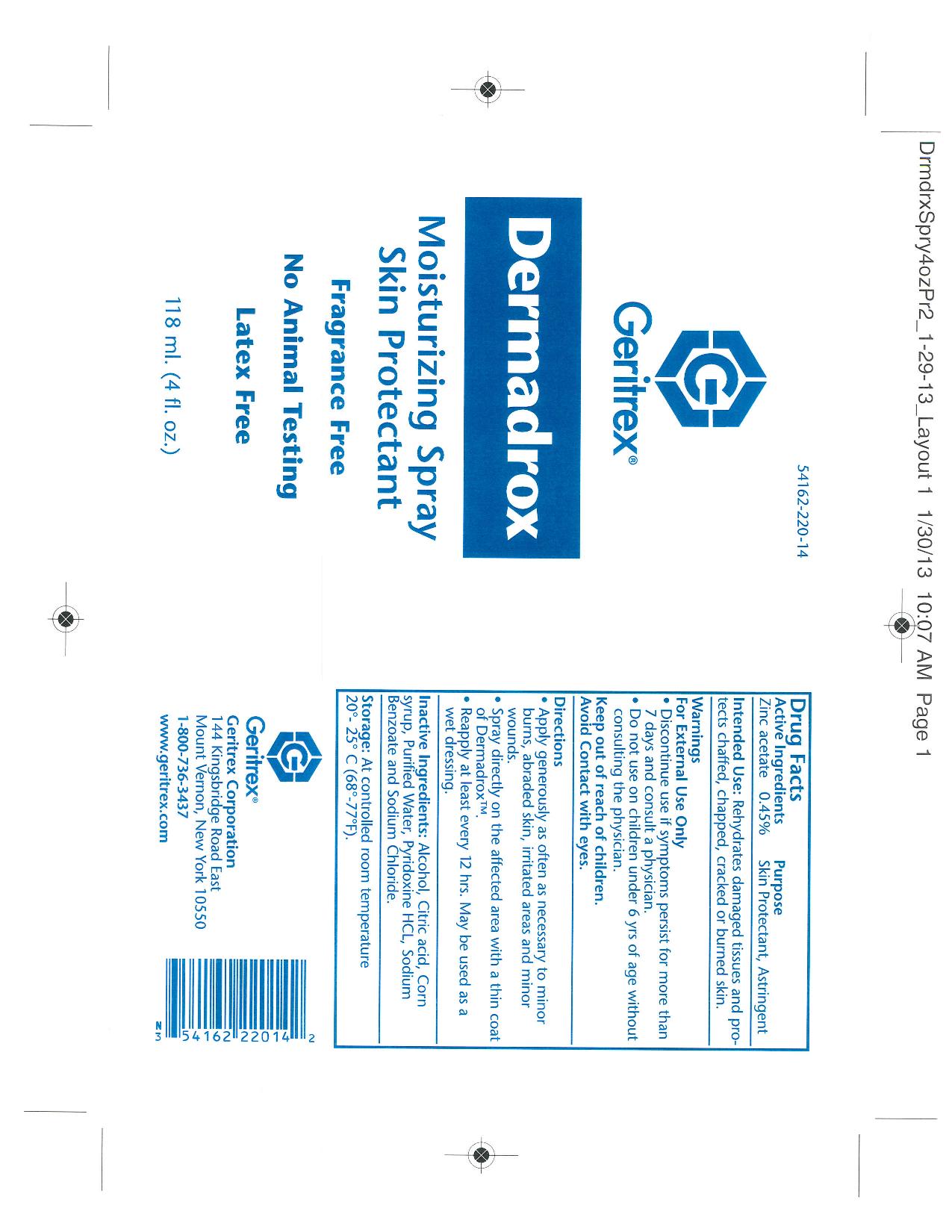 DRUG LABEL: Dermadrox
NDC: 54162-220 | Form: SPRAY
Manufacturer: Geritrex LLC
Category: otc | Type: HUMAN OTC DRUG LABEL
Date: 20150731

ACTIVE INGREDIENTS: ZINC ACETATE 0.531 g/118 mL
INACTIVE INGREDIENTS: ALCOHOL; CITRIC ACID MONOHYDRATE; CORN SYRUP; WATER; PYRIDOXINE HYDROCHLORIDE; SODIUM BENZOATE; SODIUM CHLORIDE

Dermadrox Spray

Purpose:

Skin protectant/Astringent

Intended Use:

Rehydrates damaged tissues and protects chaffed, chapped, cracked, or burned skin.

Warnings:

For External Use OnlyDiscontinue use if symptoms persist for more than 7 days and consult a physician
Do not use on children under 6 years of age without consulting a physician

Directions

Apply generously as often as necessary to minor burns, abraded skin, irritated areas and minor wounds.
Spray directly on the affected area with a thin coat of Dermadrox
Reapply at least every 12 hours. May be used as a wet dressing

Inactive Ingredients

Alcohol, Citric Acid, Corn Syrup, Purified Water, Pyridoxine HCL, Sodium Benzoate, Sodium Chloride